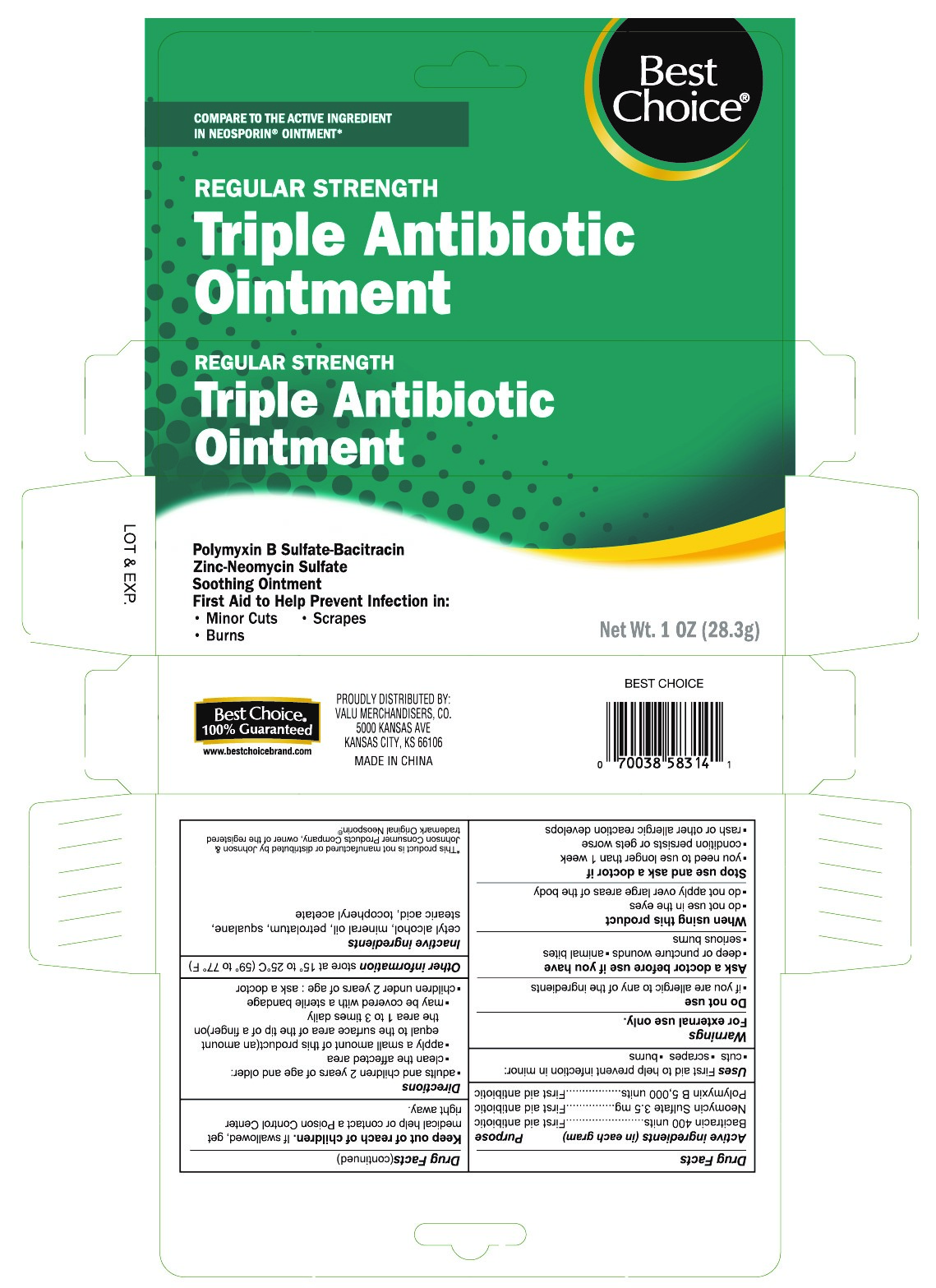 DRUG LABEL: Triple Antibiotic
NDC: 63941-831 | Form: OINTMENT
Manufacturer: Valu Merchandisers, Co.
Category: otc | Type: HUMAN OTC DRUG LABEL
Date: 20230210

ACTIVE INGREDIENTS: POLYMYXIN B SULFATE 5000 [USP'U]/1 g; NEOMYCIN SULFATE 3.5 mg/1 g; BACITRACIN ZINC 400 [USP'U]/1 g
INACTIVE INGREDIENTS: CETYL ALCOHOL; MINERAL OIL; SQUALANE; STEARIC ACID; ALPHA-TOCOPHEROL ACETATE; PETROLATUM

Best Choice Triple Antibiotic Ointment

Active ingredients

Bacitracin Zinc 400 units

Neomycin Sulfate 3.5mg

Polymyxin B Sulfate 5,000 units

Purpose

First aid antibiotic

First aid antibiotic

First aid antibiotic

Warnings

For external use only

Ask a doctor before use if you have

- serious burns
- deep or puncture wounds
- animal bites

When using this product

- do not use in the eyes
- do not apply over large areas of the body

Stop use and ask a doctor if

- you need to use more than 1 week
- condition persists or gets worse
- symptoms persist for more than 1 week or clear up and occur again within a few days.
- rash or other allergic reaction develops

Keep out of reach of children.

If swallowed, get medical help or contact a Poison Control Center right away.

Do not use

if you are allergic to any of the ingredients

Uses

First aid to help prevent infection in minor:

- cuts
- scrapes
- burns

Directions

- adults and children 2 years of age or older:
-
  - clean the affected area
  - apply a small amount of this product (an amount equal to the surface area of the tip of a finger) on the area 1 to 3 times daily
  - may be covered with a sterile bandage
- children under 2 years of age: ask a doctor

Other information

- store at 59° to 77°F

Inactive ingredients

cetyl alcohol, mineral oil, petrolatum, squalane, stearic acid, tocopheryl acetate

Package label panel

Triple Antibiotic Ointment